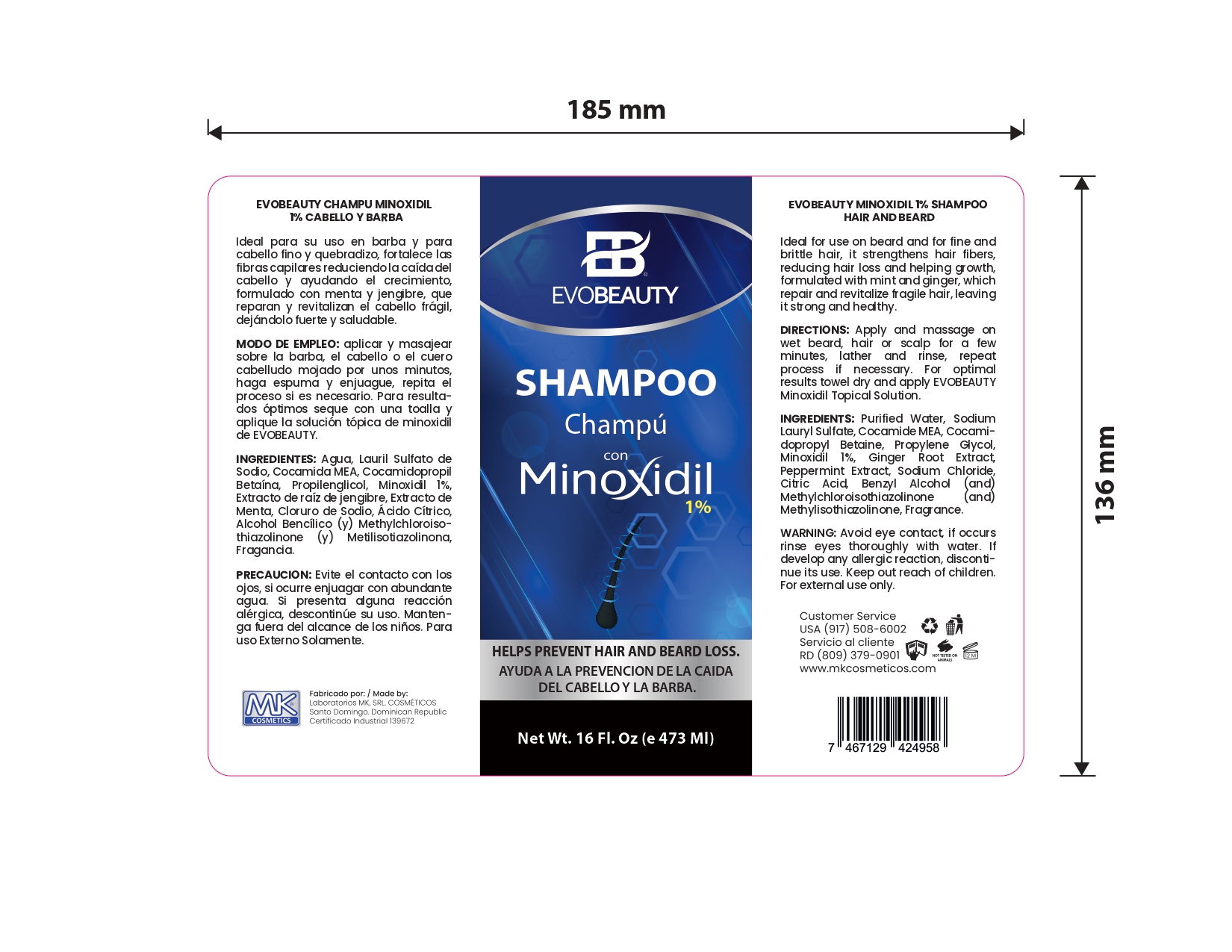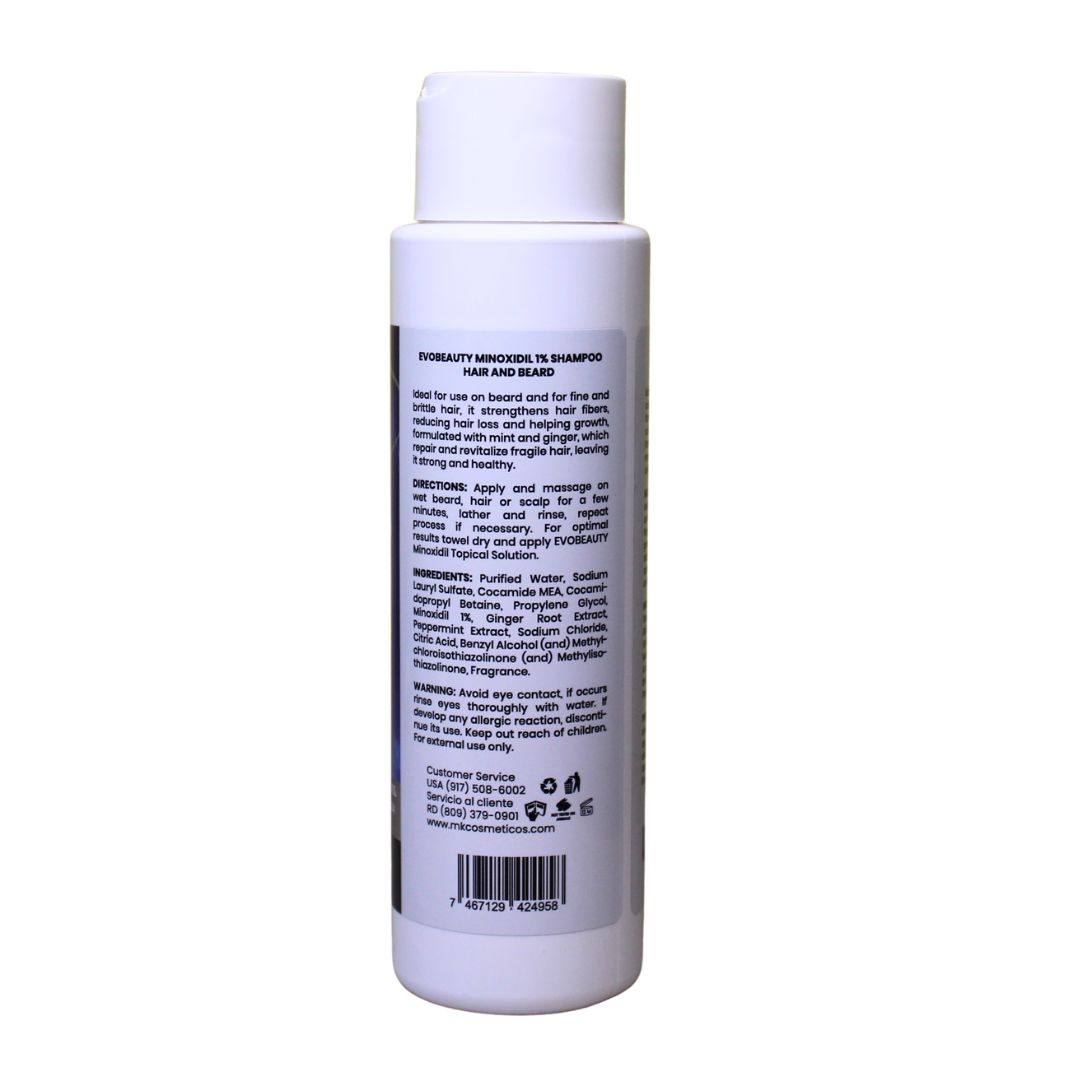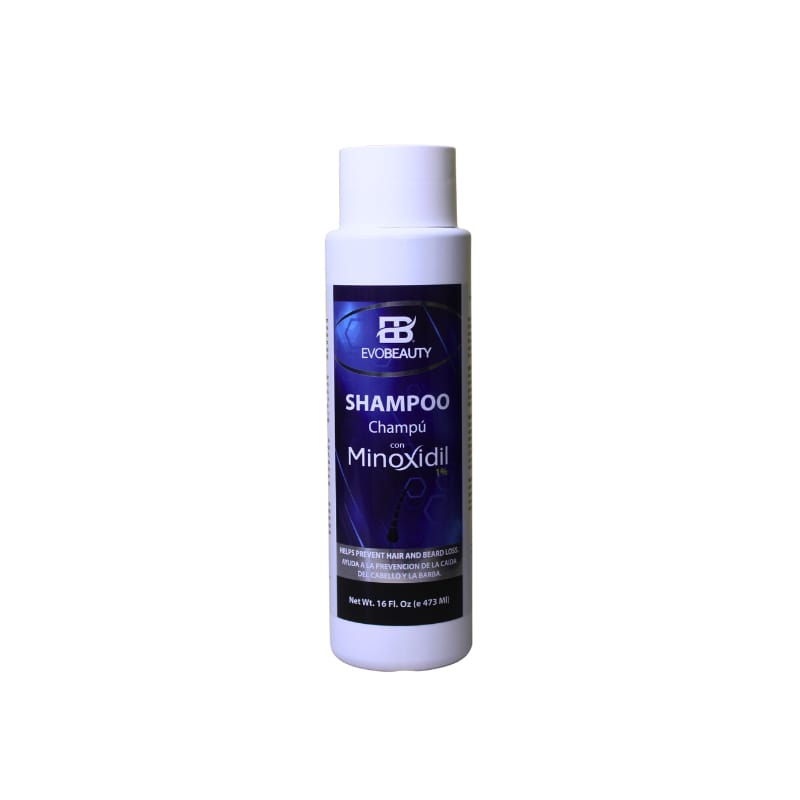 DRUG LABEL: hair champu
NDC: 87022-007 | Form: LIQUID
Manufacturer: LABORATORIO MK SRL
Category: otc | Type: HUMAN OTC DRUG LABEL
Date: 20250829

ACTIVE INGREDIENTS: MINOXIDIL 1 mg/473 mL
INACTIVE INGREDIENTS: GINGER; CITRIC ACID; PROPYLENE GLYCOL 1,2-DISTEARATE; PEPPERMINT; SODIUM CHLORIDE; SODIUM LAURYL SULFATE; COCAMIDE MEA; .ALPHA.-(.ALPHA.-AMINOPROPYL)BENZYL ALCOHOL HYDROCHLORIDE, ERYTHRO-(+/-)-; WATER; METHYLCHLOROISOTHIAZOLINONE; METHYLISOTHIAZOLINONE; BETAINE

INDICATIONS AND USAGE

Apply and massage on wet beard, hair or scalp for a few minutes, lather and rinse, repeat process if necessary

INACTIVE INGREDIENT

Purified Water, Sodium Lauryl Sulfate, Cocamide MEA, Cocamidopropyl Betaine, Propylene Glycol, Ginger Root Extract, Peppermint Extract, Sodium Chloride, Citric Acid, Benzyl Alcohol (and) Methylchloroisothiazolinone (and) Methylisothiazolinone

WARNINGS

Avoid eye contact, if occurs rinse eyes thoroughly. Do not apply to irritated scalp. If have any allergic reaction, discard its use.

INFORMATION FOR OWNERS/CAREGIVERS

Customer Service USA (917)508-6002

Customer Service RD (809)379-0900

www.mkcosmeticos.com

KEEP OUT OF REACH OF CHILDREN

Keep out reach of children, for external use only.

PURPOSE

growth and help prevent hair and beard loss. Revitalizes hair follicles and stimulates growth. it is mentioned at the front side of the box and also in the indications & usage section.

DOSAGE AND ADMINISTRATION

Apply and massage on wet beard, hair or scalp for a few minutes, lather and rinse, repeat process if necessary

PACKAGE LABEL

This is the principal panel display side of the minoxidil HAIR GROWTH SHAMPOO 1%